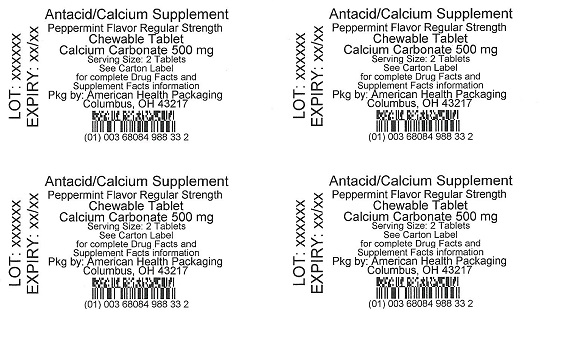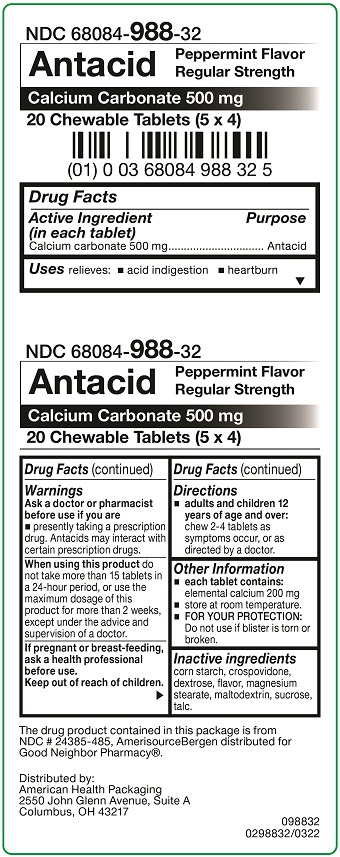 DRUG LABEL: Antacid
NDC: 68084-988 | Form: TABLET, CHEWABLE
Manufacturer: American Health Packaging
Category: otc | Type: HUMAN OTC DRUG LABEL
Date: 20241121

ACTIVE INGREDIENTS: CALCIUM CARBONATE 500 mg/1 1
INACTIVE INGREDIENTS: STARCH, CORN; CROSPOVIDONE; DEXTROSE; MAGNESIUM STEARATE; MALTODEXTRIN; SUCROSE; TALC

Antacid
Calcium Supplement
Peppermint Flavor Regular Strength

Active Ingredient (in each tablet)

Calcium carbonate 500 mg

Purpose

Antacid

Uses

relieves:

- acid indigestion
- heartburn

Warnings

Ask a doctor or pharmacist before use if you are

- presently taking a prescription drug. Antacids may interact with certain prescription drugs.

When using this product

do not take more than 15 tablets in a 24-hour period, or use the maximum dosage of this product for more than 2 weeks, except under the advice and supervision of a doctor.

Directions

- adults and children 12 years of age and over: chew 2-4 tablets as symptoms occur, or as directed by a doctor.

Other Information

- each tablet contains: elemental calcium 200 mg
- store at room temperature.
- FOR YOUR PROTECTION: Do not use if blister is torn or broken.

Inactive ingredients

corn starch, crospovidone, dextrose, flavor, magnesium stearate, maltodextrin, sucrose, talc.

Packaging Information

The drug product contained in this package is from
NDC # 24385-485, AmerisourceBergen distributed for
Good Neighbor Pharmacy®.

Distributed by:
American Health Packaging
2550 John Glenn Avenue, Suite A
Columbus, OH 43217

098832
0298832/0322

Package/Label Display Panel — Carton — 500 mg

NDC 68084- 988-32

Antacid

Peppermint Flavor
Regular Strength

Calcium Carbonate 500 mg

20 Chewable Tablets (5 x 4)

The drug product contained in this package is from
NDC # 24385-485, AmerisourceBergen distributed for
Good Neighbor Pharmacy®.

Distributed by:
American Health Packaging
2550 John Glenn Avenue, Suite A
Columbus, OH 43217

098832
0298832/0322

Package/Label Display Panel — Blister — 500 mg

Antacid/Calcium Supplement
Peppermint Flavor Regular Strength
Chewable Tablet

Calcium Carbonate 500 mg

Serving Size: 2 Tablets
See Carton Label
for complete Drug Facts and
Supplement Facts information